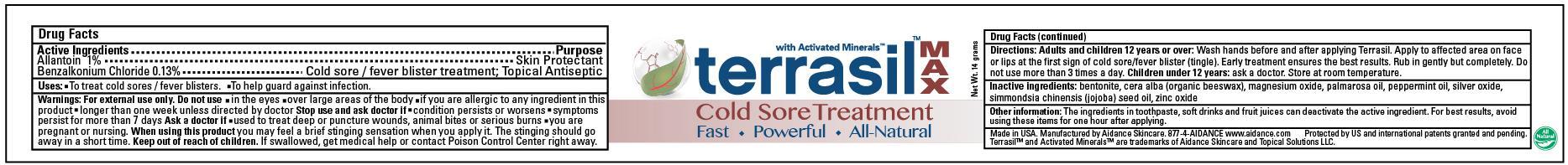 DRUG LABEL: Terrasil Cold Sore Treatment
NDC: 24909-108 | Form: OINTMENT
Manufacturer: Aidance Skincare & Topical Solutions, LLC
Category: otc | Type: HUMAN OTC DRUG LABEL
Date: 20120905

ACTIVE INGREDIENTS: ALLANTOIN 1 g/100 g; BENZALKONIUM CHLORIDE 0.13 g/100 g
INACTIVE INGREDIENTS: BENTONITE; JOJOBA OIL; MAGNESIUM OXIDE; PALMAROSA OIL; PEPPERMINT OIL; SILVER OXIDE; WHITE WAX; ZINC OXIDE

Drug Facts

Active Ingredient

Allantoin 1.0%, Benzalkonium Chloride 0.13%

Purpose

Allantoin - Skin Protectant
Benzalkonium Chloride - Cold sore / fever blister treatment; Topical Antiseptic

Uses

- To treat cold sores / fever blisters.
- To help guard against infection.

Warnings

For external use only.
Do not use in the eyes over large areas of the body if you are allergic to any ingredient in this product longer than one week unless directed by doctor
Stop use and ask doctor if condition persists or worsens symptoms persist for more than 7 days.
Ask a doctor if used to treat deep or puncture wounds, animal bites or serious burns you are pregnant or nursing.
When using this product you may feel a brief stinging sensation when you apply it. The stinging should go away in a short time.

Keep out of reach of children.

If swallowed, get medical help or contact a poison control center right away.

Directions

Adults and children 12 years or over: Wash hands before and after applying Terrasil. Apply to affected area on face or lips at the first sign of cold sore/fever blister (tingle). Early treatment ensures the best results. Rub in gently but completely. Do not use more than 3 times a day. Children under 12 years: ask a doctor. Store at room temperature.

Inactive Ingredients

bentonite, cera alba (organic beeswax), magnesium oxide, palmarosa oil, peppermint oil, silver oxide, simmondsia chinensis (jojoba) seed oil, zinc oxide

PRINCIPAL DISPLAY PANEL - 14g Label

.